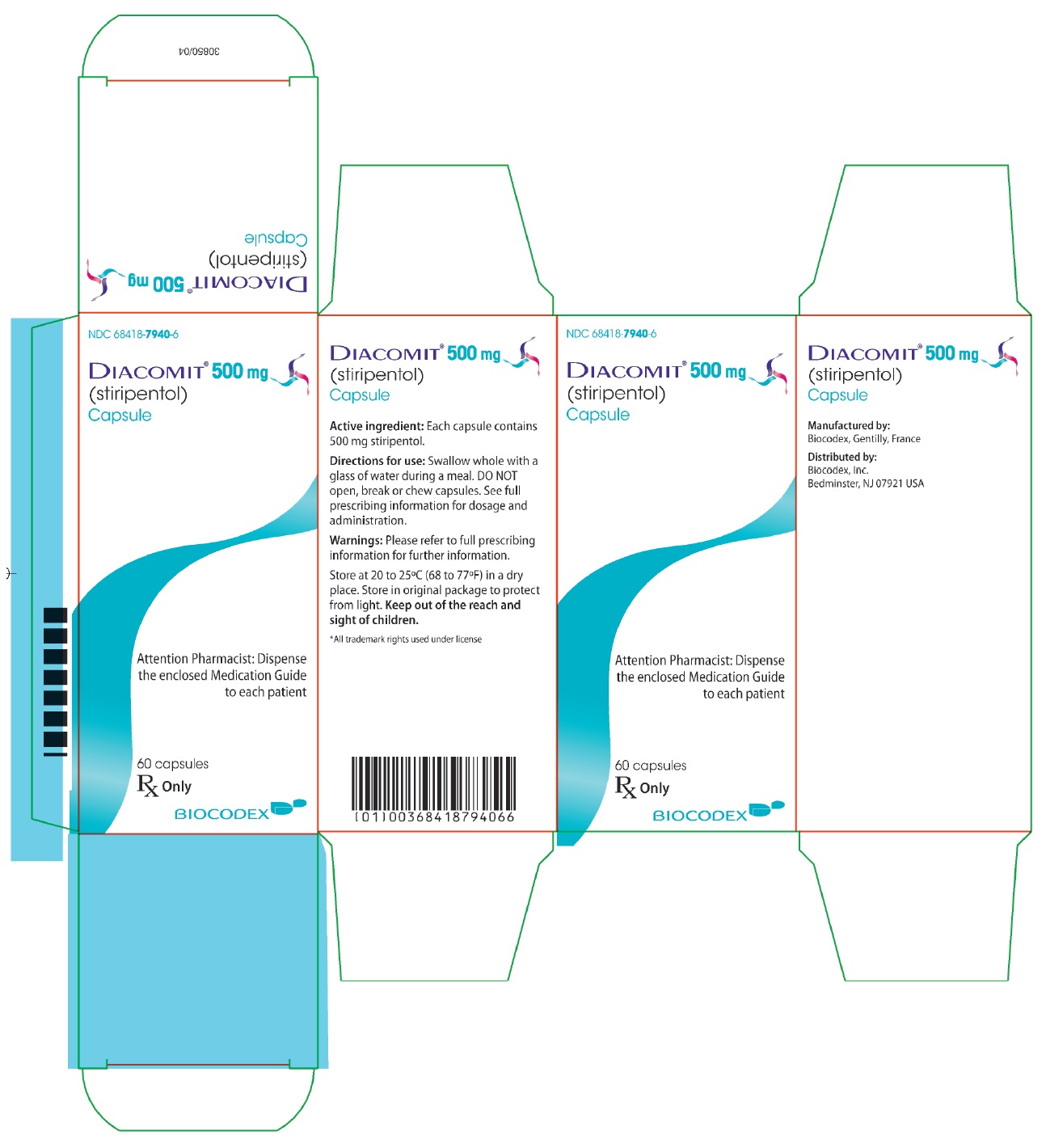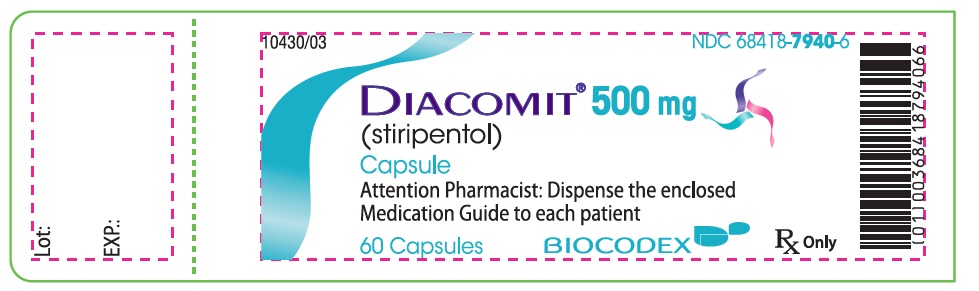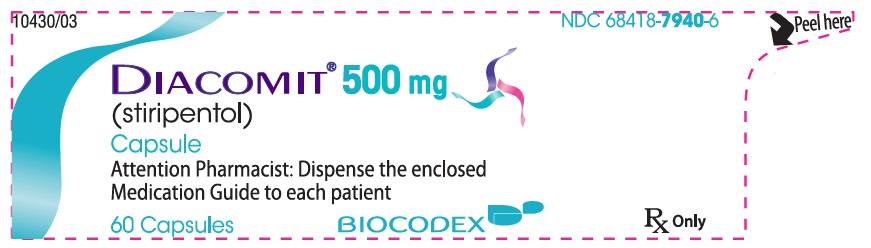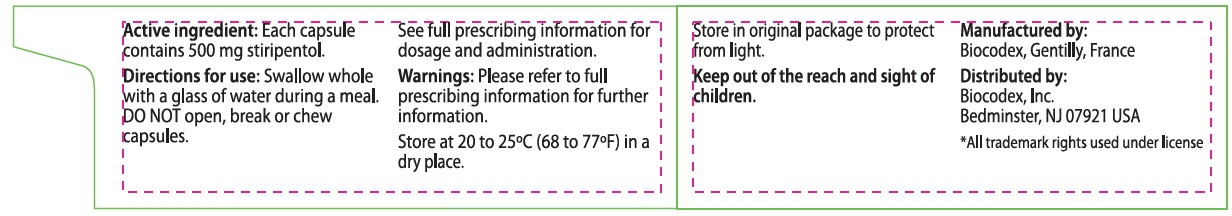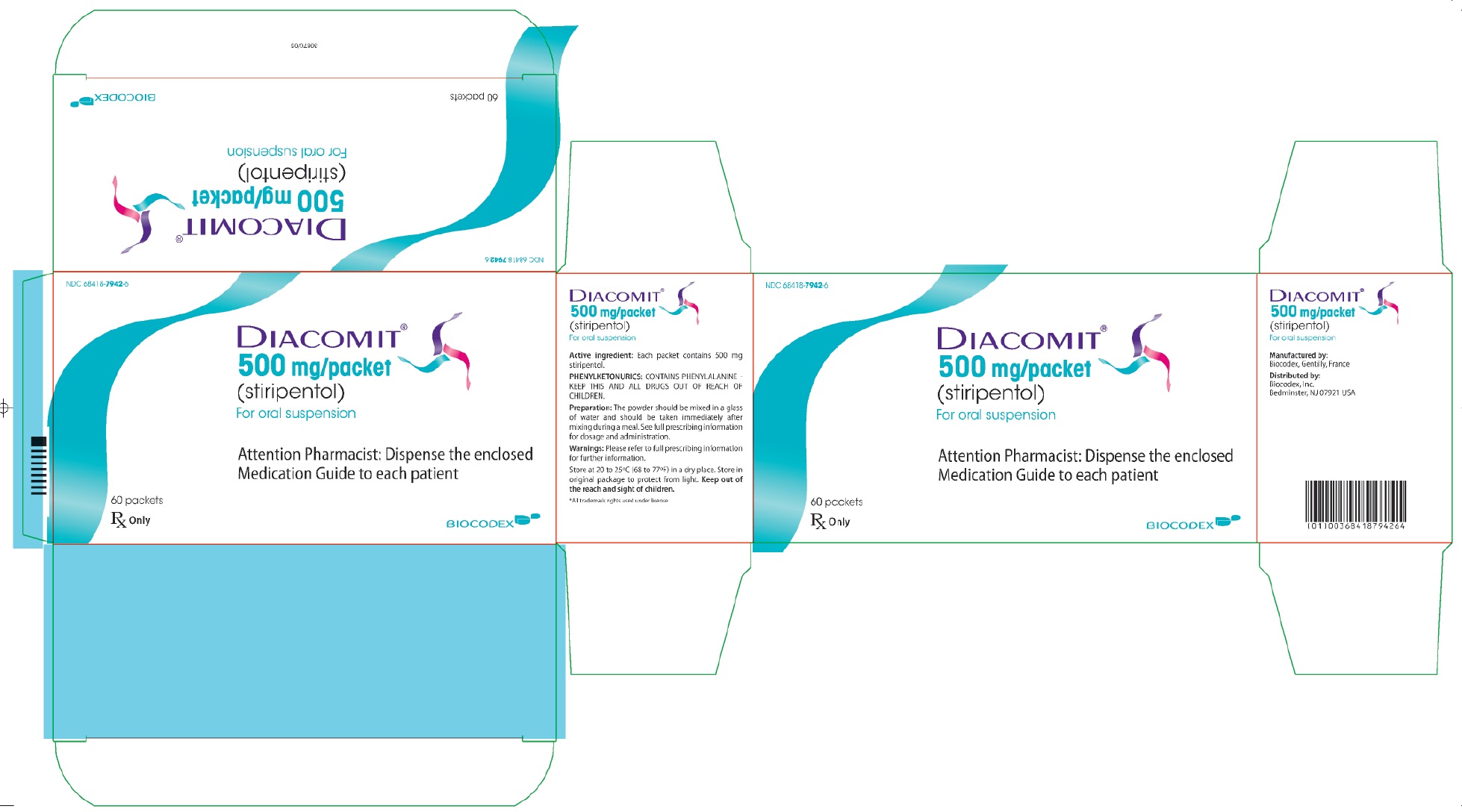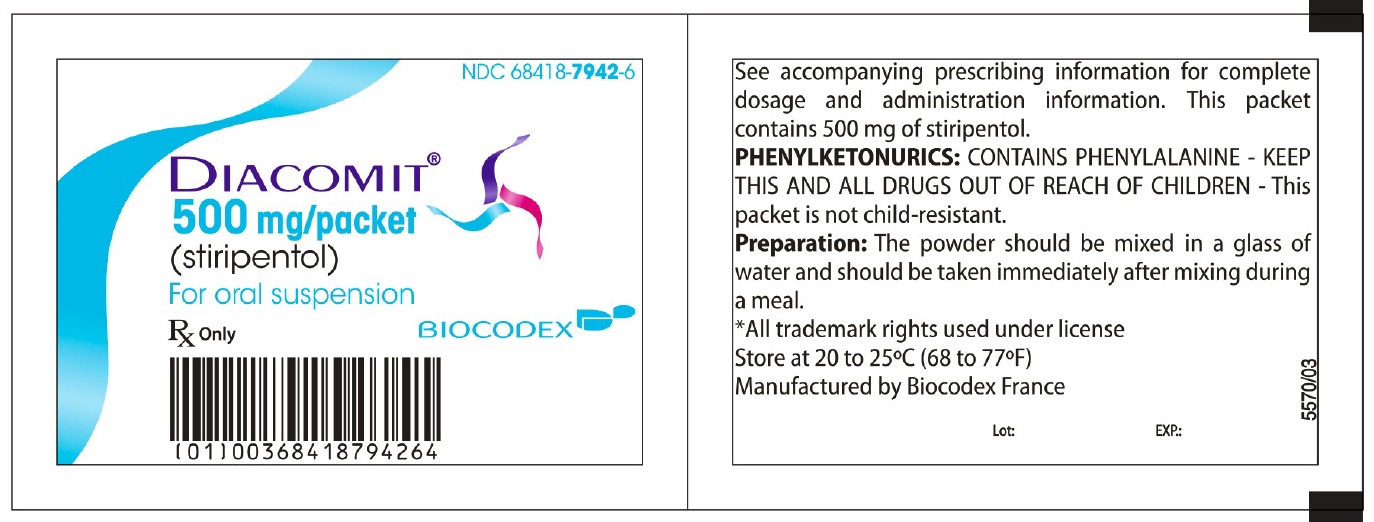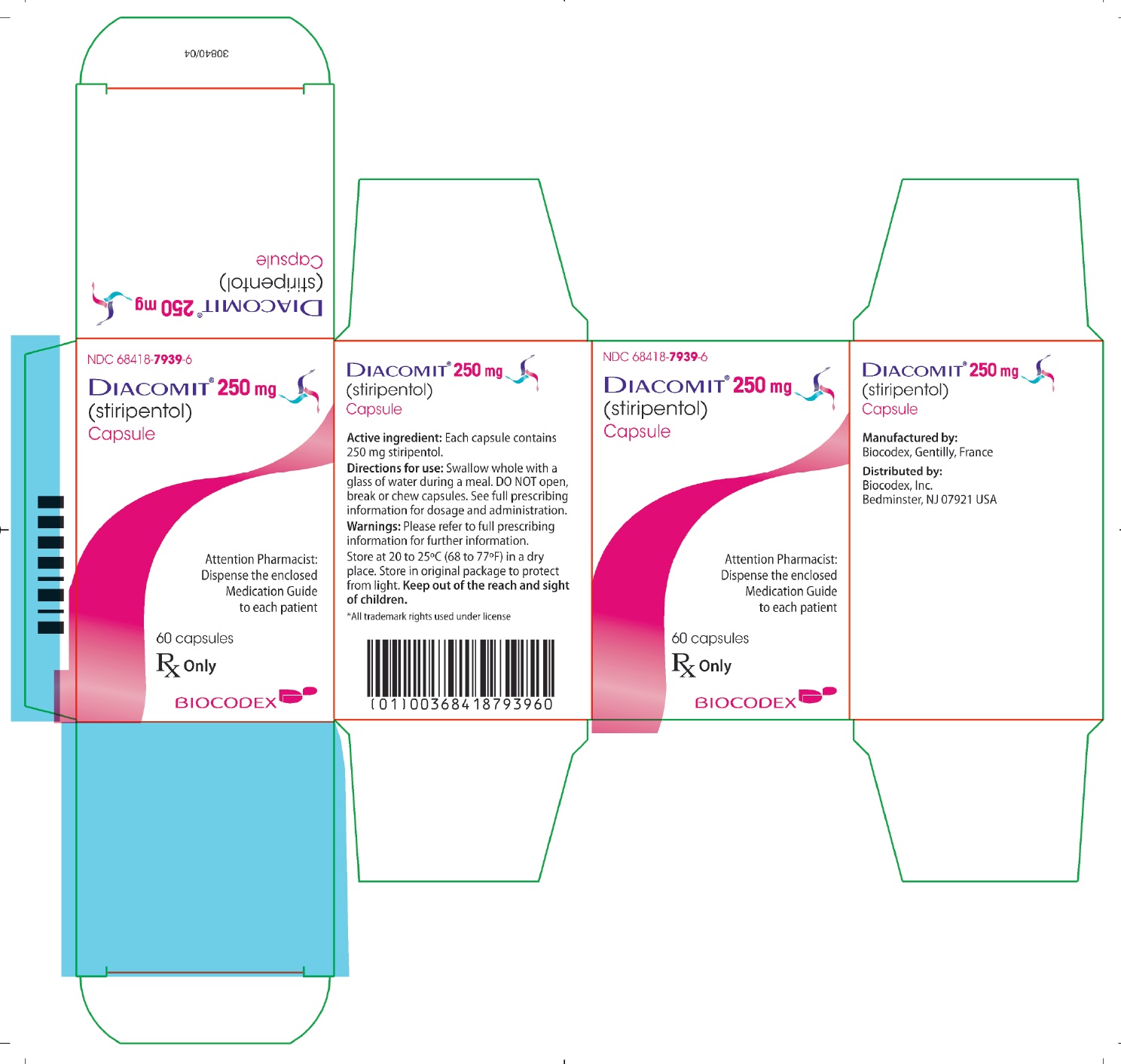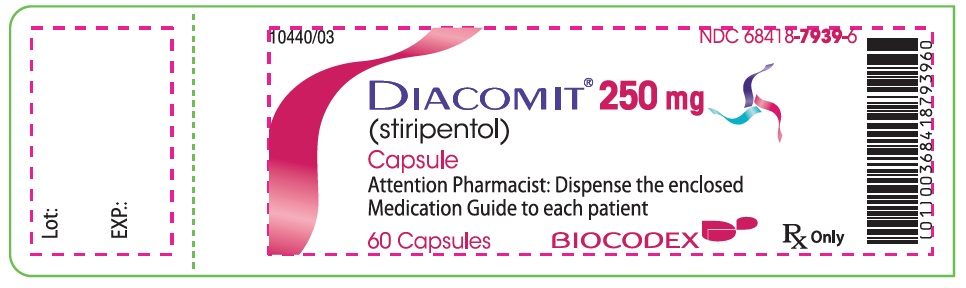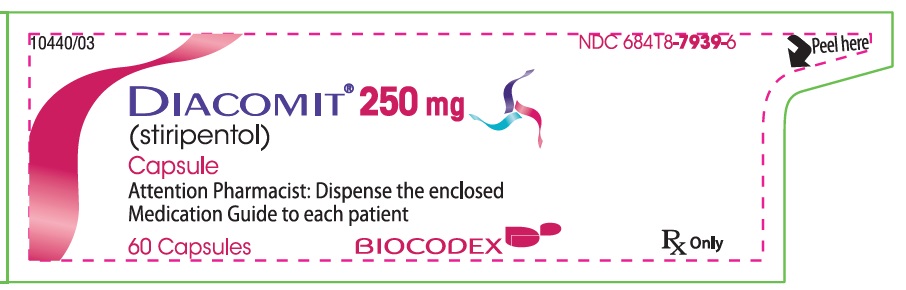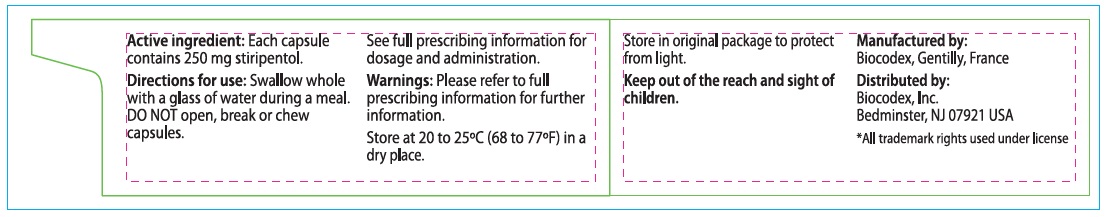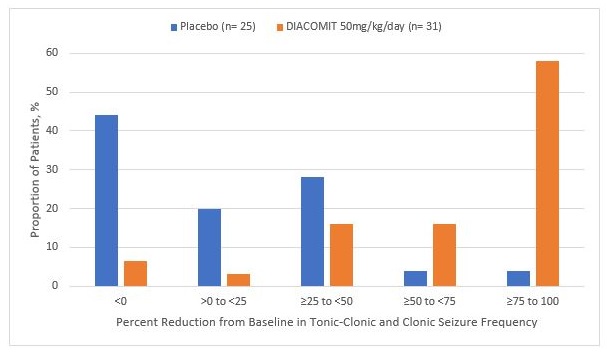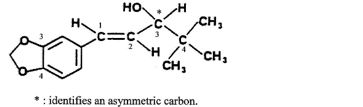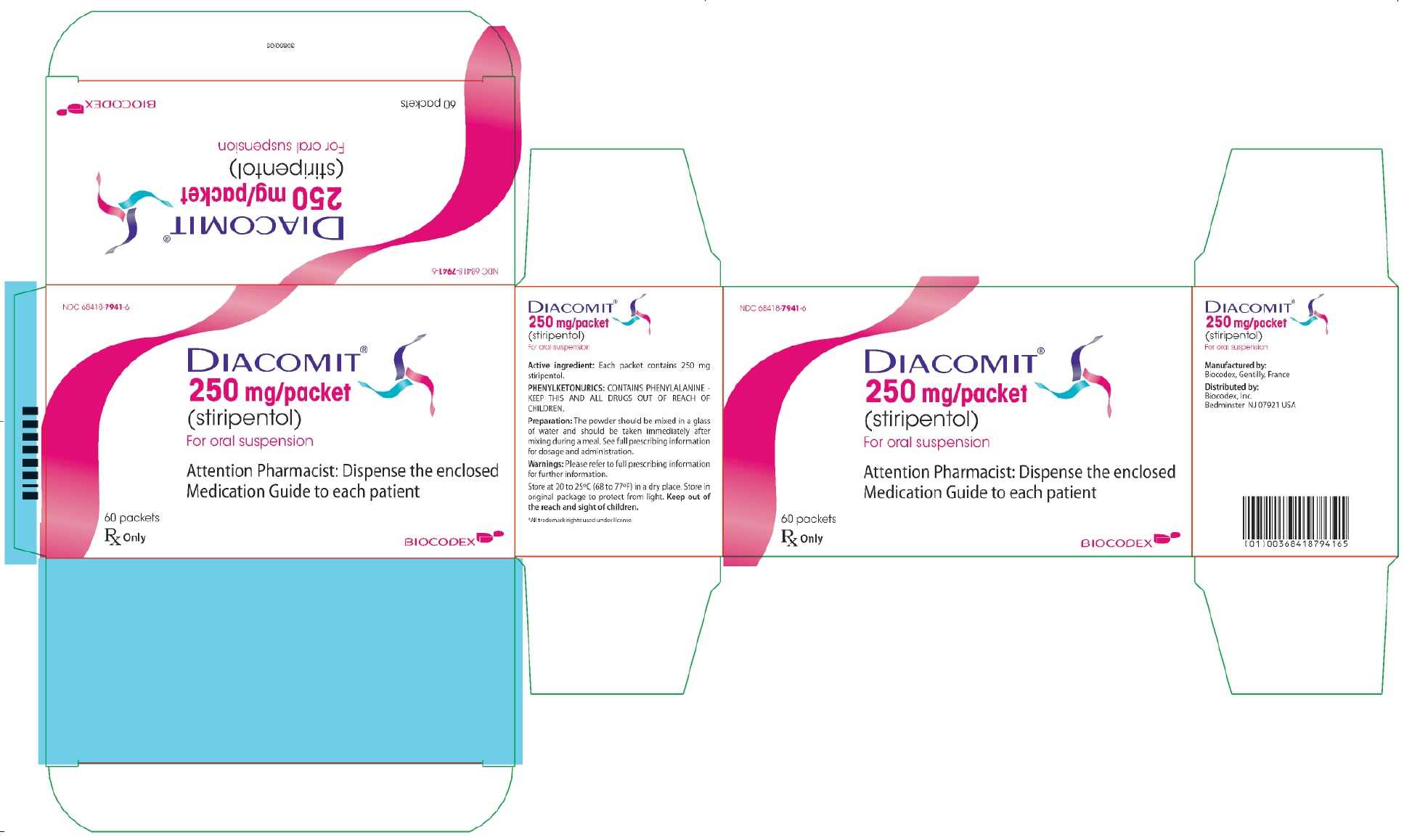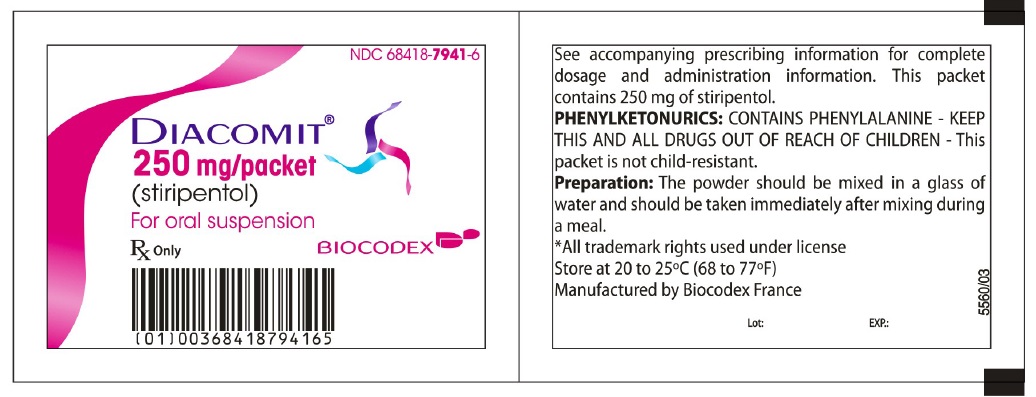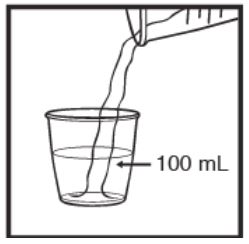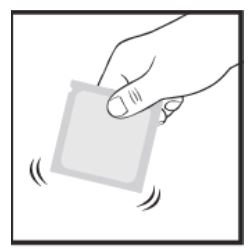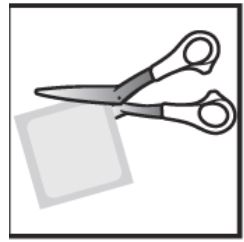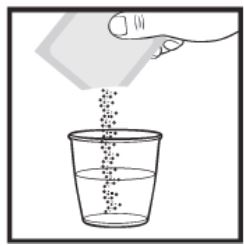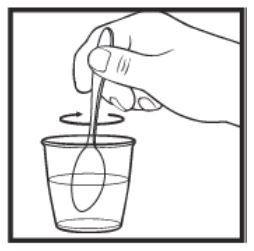 DRUG LABEL: Diacomit
NDC: 68418-7939 | Form: CAPSULE
Manufacturer: BIOCODEX, INC.
Category: prescription | Type: HUMAN PRESCRIPTION DRUG LABEL
Date: 20240605

ACTIVE INGREDIENTS: Stiripentol 250 mg/1 1
INACTIVE INGREDIENTS: FD&C Red No. 3; Gelatin, Unspecified; FD&C Blue No. 2; Magnesium Stearate; Povidone; Sodium Starch Glycolate Type A Potato; Titanium Dioxide

HIGHLIGHTS OF PRESCRIBING INFORMATION

These highlights do not include all the information needed to use DIACOMIT safely and effectively.
See full prescribing information for DIACOMIT.
DIACOMIT (stiripentol) capsules, for oral use
DIACOMIT (stiripentol) for oral suspension
Initial U.S. Approval: 2018

RECENT MAJOR CHANGES

Indications and Usage (1) 7/2022

Dosage and Administration (2.2) 7/2022

1 INDICATIONS AND USAGE

DIACOMIT is indicated for the treatment of seizures associated with Dravet syndrome in patients taking clobazam who are 6 months of age and older and weighing 7 kg or more . There are no clinical data to support the use of DIACOMIT as monotherapy in Dravet syndrome. (1)

2 DOSAGE AND ADMINISTRATION

- The dosage of DIACOMIT is 50 mg/kg/day, administered by mouth in 2 or 3 divided doses, depending on age and weight. (2.2)
- Capsules must be swallowed whole with a glass of water during a meal. Capsules should not be broken or opened. (2.3)
- Powder for suspension should be mixed in a glass of water and should be taken immediately after mixing during a meal. (2.3)
- Reduce dose or discontinue dose gradually. (2.5)

3 DOSAGE FORMS AND STRENGTHS

- Capsule: 250 mg or 500 mg (3)
- For Oral Suspension: 250 mg or 500 mg (3)

4 CONTRAINDICATIONS

None (4)

5 WARNINGS AND PRECAUTIONS

- Somnolence: Monitor for somnolence, particularly when DIACOMIT is used concomitantly with other CNS depressants; If somnolence occurs during co-administration with clobazam, consider an initial reduction of clobazam by 25%. (5.1)
- Decreased Appetite and Decreased Weight: the weight of patients and the growth rate of pediatric patients should be carefully monitored. (5.2)
- Neutropenia and Thrombocytopenia: Blood counts should be obtained prior to starting treatment with DIACOMIT and then every 6 months. (5.3)
- Withdrawal: DIACOMIT should be gradually withdrawn to minimize the risk of increased seizure frequency and status epilepticus. (5.4)
- Risks in Patients with Phenylketonuria (PKU): DIACOMIT for oral suspension contains phenylalanine; consider total daily intake before prescribing to patients with PKU. (5.5)
- Suicidal Behavior and Ideation: Monitor for suicidal thoughts or behaviors. (5.6)

6 ADVERSE REACTIONS

Adverse reactions that occurred in at least 10% of DIACOMIT-treated patients and more frequently than on placebo were somnolence, decreased appetite, agitation, ataxia, weight decreased, hypotonia, nausea, tremor, dysarthria, and insomnia. (6.1)
To report SUSPECTED ADVERSE REACTIONS, contact BIOCODEX at 1-866-330-3050 or FDA at 1-800-FDA-1088 or www.fda.gov/medwatch.

7 DRUG INTERACTIONS

- DIACOMIT increases the plasma concentration of clobazam and its metabolite through metabolic inhibition of CYP3A4 and CYP2C19. Consider dose reduction of clobazam in case of adverse reactions. (7.1)
- Substrates of CYP2C8, CYP2C19, P-gp and BCRP may require a dose reduction. (7.1)
- Substrates of CYP1A2, CYP2B6 and CYP3A4 may require a dose adjustment. (7.1)
- Strong inducers of CYP1A2, CYP3A4 or CYP2C19: Consider dose increase of DIACOMIT. (7.2)

8 USE IN SPECIFIC POPULATIONS

- Pregnancy: Based on animal data, may cause fetal harm. (8.1)

FULL PRESCRIBING INFORMATION

1 INDICATIONS AND USAGE

DIACOMIT is indicated for the treatment of seizures associated with Dravet syndrome (DS) in patients taking clobazam who are 6 months of age and older and weighing 7 kg or more. There are no clinical data to support the use of DIACOMIT as monotherapy in Dravet syndrome.

2 DOSAGE AND ADMINISTRATION

2.1 Laboratory Tests Prior to First Dose of DIACOMIT

Hematologic testing should be obtained prior to starting treatment with DIACOMIT [see Warnings and Precautions (5.3)].

2.2 Dosing Information

The recommended oral dosage of DIACOMIT is 50 mg/kg/day, administered in 2 or 3 divided doses (i.e., 16.67 mg/kg three times daily or 25 mg/kg twice daily), depending on the patient’s age and body weight as shown in Table 1. If the exact dosage is not achievable given the available strengths, round to the nearest possible dosage, which is usually within 50 mg to 150 mg of the recommended 50 mg/kg/day. A combination of the two DIACOMIT strengths can be used to achieve this dosage. The maximum recommended total dosage is 3,000 mg/day.

Table 1. Recommended Dosage for Patients 6 Months of Age and Older Weighing 7 kg or More with Dravet Syndrome

Age of Patient | Body Weight | Dosing Regimen; (administered by mouth in equally divided doses) | Total Daily Dose
6 months to less than 1 year | 7 kg and above | 25 mg/kg twice dailya,b | 50 mg/kg/day
1 year and above | 7 kg to less than 10 kg | 25 mg/kg twice dailyb | 50 mg/kg/day
1 year and above | 10 kg and above | 25 mg/kg twice daily or; 16.67 mg/kg three times daily | 50 mg/kg/day; Maximum daily dose is 3000 mg

a Dosing frequency should not exceed twice daily to limit free water administration.

b Dosing frequency should not exceed twice daily to avoid overexposures.

2.3 Important Administration Instructions

DIACOMIT Capsules
DIACOMIT capsules must be swallowed whole with a glass of water during a meal. Capsules should not be broken or opened.

DIACOMIT for Oral Suspension
DIACOMIT should be mixed in a glass of water (100 mL) and should be taken immediately after mixing during a meal. To be sure there is no medicine left in the glass, add a small amount of water (25 mL) to the drinking cup and drink all of the mixture [see Instructions for Use].

2.4 Missed Dose

A missed dose should be taken as soon as possible. If it is almost time for the next dose, the missed dose should not be taken. Instead, the next scheduled dose should be taken. Doses should not be doubled.

2.5 Gradual Withdrawal

As is advisable for most antiepileptic drugs, if DIACOMIT treatment is discontinued, the drug should be withdrawn gradually to minimize the risk of increased seizure frequency and status epilepticus [see Warnings and Precautions (5.4)].

In situations where rapid withdrawal of DIACOMIT is medically required, appropriate monitoring is recommended.

3 DOSAGE FORMS AND STRENGTHS

Capsules

- 250 mg: size 2, pink, and imprinted with “Diacomit” and “250mg”
- 500 mg: size 0, white, and imprinted with “Diacomit” and “500mg”

For Oral Suspension

- Pale pink fruit flavored powder packaged in packets. Each packet contains either 250 mg or 500 mg of stiripentol

4 CONTRAINDICATIONS

None.

5 WARNINGS AND PRECAUTIONS

5.1 Somnolence

DIACOMIT can cause somnolence. In controlled studies in patients with Dravet syndrome, the incidence of somnolence was 67% in DIACOMIT-treated patients, compared to 23% in patients on placebo. All patients in both groups were on concomitant clobazam, which is also known to cause somnolence. Co-administration of DIACOMIT with clobazam results in increased levels of clobazam and its active metabolite [see Drug Interactions (7.1)]. Other central nervous system CNS depressants, including alcohol, could potentiate the somnolence effect of DIACOMIT.

Prescribers should monitor patients for somnolence. If somnolence occurs during co-administration with clobazam, consider an initial reduction of clobazam by 25%. If somnolence persists, further clobazam reduction by an additional 25% should be considered, as should adjustment of the dosage of other concomitant anticonvulsant drugs with sedating properties. Prescribers should caution patients against engaging in hazardous activities requiring mental alertness, such as operating dangerous machinery or motor vehicles, until the effect of DIACOMIT on mental alertness is known.

5.2 Decreased Appetite and Decreased Weight

DIACOMIT can cause decreases in appetite and weight. In controlled studies in patients with Dravet syndrome, the incidence of decreased appetite was 46% in DIACOMIT-treated patients, compared to 10% in patients on placebo. The incidence of decreased weight was 27% in DIACOMIT-treated patients, compared to 6% in patients on placebo. Nausea and vomiting also occurred more frequently in DIACOMIT-treated patients [see Adverse Reactions (6.1)]. Given the frequency of these adverse reactions, the growth of pediatric patients treated with DIACOMIT should be carefully monitored. In some cases, decreasing the dose of concomitant valproate by 30% per week can reduce the decrease in appetite and weight.

5.3 Neutropenia and Thrombocytopenia

DIACOMIT can cause a significant decline in neutrophil count. In controlled studies in patients with Dravet syndrome, there were 31 patients treated with DIACOMIT who had both a baseline and end-of-study neutrophil count obtained. A decrease in neutrophil count from normal at baseline to less than 1500 cells/mm^3 during the trial was observed in 13% of these DIACOMIT- treated patients, but not in any placebo-treated patients.

DIACOMIT can cause a significant decline in platelet count. In controlled studies in patients with Dravet syndrome, there were 31 patients treated with DIACOMIT who had both a baseline and end-of-study platelet count. A decrease in platelet count from normal at baseline to less than 150,000/µL during the trial was observed in 13% of these DIACOMIT-treated patients, but not in any placebo-treated patients.

Hematologic testing should be obtained prior to starting treatment with DIACOMIT, and then every 6 months.

5.4 Withdrawal Symptoms

As with most antiepileptic drugs, DIACOMIT should generally be withdrawn gradually to minimize the risk of increased seizure frequency and status epilepticus.

In situations where rapid withdrawal of DIACOMIT is required (e.g., in the setting of a serious adverse reaction), appropriate monitoring is recommended.

5.5 Risks in Patients with Phenylketonuria

Phenylalanine can be harmful to patients with phenylketonuria (PKU). DIACOMIT for oral suspension contains phenylalanine, a component of aspartame. Each 250 mg packet contains 1.40 mg phenylalanine; each 500 mg packet contains 2.80 mg phenylalanine. Before prescribing DIACOMIT for oral Suspension to a patient with PKU, consider the combined daily amount of phenylalanine from all sources, including DIACOMIT for oral Suspension.

DIACOMIT capsules do not contain phenylalanine.

5.6 Suicidal Behavior and Ideation

AEDs, including DIACOMIT, increase the risk of suicidal thoughts or behavior in patients taking these drugs for any indication. Patients treated with any AED for any indication should be monitored for the emergence or worsening of depression, suicidal thoughts or behavior, and/or any unusual changes in mood or behavior.

Pooled analyses of 199 placebo-controlled clinical trials (mono- and adjunctive therapy) of 11 different AEDs showed that patients randomized to one of the AEDs had approximately twice the risk (adjusted relative risk 1.8, 95% confidence interval [CI]:1.2, 2.7) of suicidal thinking or behavior compared to patients randomized to placebo. In these trials, which had a median treatment duration of 12 weeks, the estimated incidence rate of suicidal behavior or ideation among 27,863 AED treated patients was 0.43%, compared to 0.24% among 16,029 placebo treated patients, representing an increase of approximately one case of suicidal thinking or behavior for every 530 patients treated. There were four suicides in drug treated patients in the trials and none in placebo treated patients, but the number is too small to allow any conclusion about drug effect on suicide.

The increased risk of suicidal thoughts or behavior with AEDs was observed as early as one week after starting drug treatment with AEDs and persisted for the duration of treatment assessed. Because most trials included in the analysis did not extend beyond 24 weeks, the risk of suicidal thoughts or behavior beyond 24 weeks could not be assessed.

The risk of suicidal thoughts or behavior was generally consistent among drugs in the data analyzed. The finding of increased risk with AEDs of varying mechanisms of action and across a range of indications suggests that the risk applies to all AEDs used for any indication. The risk did not vary substantially by age (5-100 years) in the clinical trials analyzed. Table2 shows absolute and relative risk by indication for all evaluated AEDs.

Table 2. Risk by Indication for Antiepileptic Drugs in the Pooled Analysis
Indication | Placebo Patients with Events per 1000 Patients | Drug Patients with Events per 1000 Patients | Relative Risk: Incidence of Drug Events in Drug Patients/Incidence in Placebo Patients | Risk Difference: Additional Drug Patients with Events per 1000 Patients
Epilepsy | 1.0 | 3.4 | 3.5 | 2.4
Psychiatric | 5.7 | 8.5 | 1.5 | 2.9
Other | 1.0 | 1.8 | 1.9 | 0.9
Total | 2.4 | 4.3 | 1.8 | 1.9

The relative risk for suicidal thoughts or behavior was higher in clinical trials for epilepsy than in clinical trials for psychiatric or other conditions, but the absolute risk differences were similar for the epilepsy and psychiatric indications.

Anyone considering prescribing DIACOMIT or any other AED must balance the risk of suicidal thoughts or behavior with the risk of untreated illness. Epilepsy and many other illnesses for which AEDs are prescribed are themselves associated with morbidity and mortality and an increased risk of suicidal thoughts and behavior. Should suicidal thoughts and behavior emerge during treatment, the prescriber needs to consider whether the emergence of these symptoms in any given patient may be related to the illness being treated.

Patients, their caregivers, and families should be informed that AEDs increase the risk of suicidal thoughts and behavior and should be advised of the need to be alert for the emergence or worsening of the signs and symptoms of depression, any unusual changes in mood or behavior, or the emergence of suicidal thoughts, behavior, or thoughts about self-harm. Behaviors of concern should be reported immediately to healthcare providers.

6 ADVERSE REACTIONS

The following serious or otherwise clinically significant adverse reactions are described elsewhere in the labeling:

- Somnolence [see Warnings and Precautions (5.1)]
- Decreased Appetite and Decreased Weight [see Warnings and Precautions (5.2)]
- Neutropenia and Thrombocytopenia [see Warnings and Precautions (5.3)]
- Withdrawal Symptoms [see Warnings and Precautions (5.4)]
- Risks in Patients with Phenylketonuria [see Warnings and Precautions (5.5)]
- Suicidal Behavior and Ideation [see Warnings and Precautions (5.6)]

6.1 Clinical Trials Experience

Because clinical trials are conducted under widely varying conditions, adverse reaction rates observed in the clinical trials of a drug cannot be directly compared to rates in clinical trials of another drug, and may not reflect the rates observed in practice.

During its development for the treatment of seizures associated with Dravet syndrome, DIACOMIT was administered to 55 healthy male volunteers and 438 patients with Dravet syndrome, including 310 patients treated for 12 months or more. The conditions and duration of exposure varied greatly, and included single- and multiple-dose clinical pharmacology studies in healthy male volunteers, 2 randomized, double-blind, placebo-controlled, 12-week studies in patients with Dravet syndrome (Study 1 and Study 2), and open-label long-term studies.

In Study 1 and Study 2, 33 patients received DIACOMIT and 31 patients received placebo for a treatment duration of 8 weeks [see Clinical Studies (14)]. Adverse reactions from these trials are presented below. Approximately 53% of patients were female and the mean age was 9.2 years. All patients were taking clobazam and valproate.

There were 2 patients in whom adverse reactions led to discontinuation of DIACOMIT treatment: one patient had an adverse reaction of status epilepticus; the second patient had drowsiness, balance impaired and sialorrhea.

The most common adverse reactions, occurring in at least 10% of DIACOMIT-treated patients and more frequently than on placebo, included somnolence (67%), decreased appetite (45%), agitation (27%), ataxia (27%), weight decreased (27%), hypotonia (24%), nausea (15%), tremor (15%), dysarthria (12%), and insomnia (12%).

Table 3 lists the adverse reactions that occurred in 5% or more of DIACOMIT-treated patients and at a rate greater than in patients on placebo in the 2 randomized, double-blind, placebo-controlled, clinical trials in patients with Dravet syndrome (Study 1 and Study 2).

Table 3. Adverse Reactions in 5% or More of DIACOMIT-Treated Patients and More Frequently than on Placebo in Patients with Dravet Syndrome (Study 1 and Study 2)
 | Study 1 and 2 – Pooled Total
 | DIACOMIT (50mg/kg/day) | Placebo
Adverse Reactions | N=33% | N=31%
Gastrointestinal disorders
Nausea | 15 | 3
Vomiting | 9 | 0
Salivary hypersecretion | 6 | 0
General disorders and administration site conditions
Fatigue | 9 | 3
Pyrexia | 6 | 3
Infections and infestations
Bronchitis | 6 | 0
Nasopharyngitis | 6 | 0
Investigations
Weight decreased | 27 | 6
Weight increased | 6 | 3
Metabolism and nutrition disorders
Decreased appetite | 46 | 10
Nervous system disorders
Somnolence | 67 | 23
Ataxia | 27 | 23
Hypotonia | 18 | 13
Tremor | 15 | 10
Dysarthria | 12 | 0
Psychiatric disorders
Agitation | 27 | 16
Insomnia | 12 | 7
Aggression | 9 | 0

Adverse Reactions in Pediatric Patients 6 months to Less Than 2 Years of Age

In five open-label studies including pediatric patients 6 months to less than 2 years of age with Dravet syndrome, a total of 106 patients received DIACOMIT, with 81 patients exposed for at least 6 months, and 69 patients exposed for at least 1 year. Adverse reactions in pediatric patients with Dravet syndrome who were 6 months to less than 2 years of age were similar to those seen in patients in Study 1 and Study 2.

7 DRUG INTERACTIONS

7.1 Effect of DIACOMIT on Other Drugs

CYP1A2, CYP2B6, CYP3A4, CYP2C8, CYP2C19, P-glycoprotein (P-gp) and Breast Cancer Resistance Protein (BCRP) Substrates

In vitro data show that stiripentol is both an inhibitor and inducer of CYP1A2, CYP2B6, and CYP3A4. Because of potential drug-drug interactions, consider dose adjustment of CYP1A2 substrates (e.g., theophylline, caffeine), CYP2B6 substrates (e.g., sertraline, thiotepa), and CYP3A4 substrates (e.g., midazolam, triazolam, quinidine), as clinically appropriate, when administered concomitantly with DIACOMIT.

Because of potential inhibition of enzyme/transporter activity, consider a reduction in dosage of substrates of CYP2C8, CYP2C19 (e.g., diazepam, clopidogrel), P-gp (e.g., carbamazepine), and BCRP (e.g., methotrexate, prazosin, glyburide), if adverse reactions are experienced when administered concomitantly with DIACOMIT.

Clobazam
Co-administration of DIACOMIT (which inhibits CYP 3A4 and 2C19) with clobazam results in increased plasma concentrations of clobazam (a substrate of CYP3A4) and norclobazam, the active metabolite of clobazam (a substrate of CYP2C19) [see Clinical Pharmacology (12.3)]. This may increase the risk of clobazam-related adverse reactions. Consider a reduction in dosage of clobazam if adverse reactions are experienced when co-administered with DIACOMIT [see Warnings and Precautions (5.1)].

7.2 Effect of Other Drugs on DIACOMIT

Induction-based interactions leading to decreases in DIACOMIT concentrations are possible when co-administered with a potent CYP1A2, CYP3A4, or CYP2C19 inducer, such as rifampin, phenytoin, phenobarbital and carbamazepine, as these enzymes all metabolize stiripentol. Concomitant use of strong inducers with DIACOMIT should be avoided, or dosage adjustments should be made.

7.3 CNS Depressants and Alcohol

Concomitant use of DIACOMIT with other CNS depressants, including alcohol, may increase the risk of sedation and somnolence [see Warnings and Precautions (5.1)].

8 USE IN SPECIFIC POPULATIONS

8.1 Pregnancy

Pregnancy Exposure Registry
There is a pregnancy exposure registry that monitors pregnancy outcomes in women exposed to AEDs, such as DIACOMIT, during pregnancy. Physicians are advised to recommend that pregnant patients taking DIACOMIT enroll in the North American Antiepileptic Drug (NAAED) Pregnancy Registry. This can be done by calling the toll free number 1-888-233-2334, and must be done by patients themselves or their caregiver. Information on the registry can also be found at the website http://www.aedpregnancyregistry.org/.

Risk Summary
There are no adequate data on the developmental risks associated with the use of DIACOMIT in pregnant women. Administration of stiripentol to pregnant animals produced evidence of developmental toxicity, including increased incidences of fetal malformations, increased embryofetal and pup mortality, and decreased embryofetal and pup growth, at maternal doses lower than the recommended clinical dose [see Animal Data].

The background risk of major birth defects and miscarriage in Dravet syndrome is unknown. In the U.S. general population, the estimated background risk of major birth defects and miscarriage in clinically recognized pregnancies is 2 to 4% and 15 to 20%, respectively.

Data

Animal Data
Oral administration of stiripentol (0, 50, 200, or 800 mg/kg/day) to pregnant mice throughout the period of organogenesis resulted in increased embryofetal mortality and decreased fetal body weights at all doses and an increased incidence of malformations at the high dose, with no evidence of maternal toxicity. The lowest effect dose for developmental toxicity in mice (50 mg/kg/day) was less than the recommended human dose (RHD) of 50 mg/kg/day on a body surface area (mg/m^2) basis.

Oral administration of stiripentol (0, 50, 200, or 800 mg/kg/day) to pregnant rabbits throughout organogenesis resulted in increased embryofetal mortality at the mid and high dose and decreased fetal body weights at all doses. The mid and high doses were associated with maternal toxicity. The lowest effect dose for developmental toxicity in rabbits (50 mg/kg/day) was less than the RHD on a mg/m^2 basis.

Oral administration of stiripentol (0, 50, 200, or 800 mg/kg/day) to rats throughout pregnancy and lactation resulted in decreased pup survival, decreased pup body weights at birth and throughout lactation, and deficits in pup reflex development at the high dose, which was also associated with maternal toxicity. The no-effect dose for pre- and postnatal developmental toxicity in rats (200 mg/kg) was less than the RHD on a mg/m^2 basis.

8.2 Lactation

Risk Summary
There are no data on the presence of stiripentol in human milk, the effects on the breastfed infant, or the effects on milk production.

The developmental and health benefits of breastfeeding should be considered along with the mother’s clinical need for DIACOMIT and any potential adverse effects on the breastfed infant from DIACOMIT or from the underlying maternal condition.

8.4 Pediatric Use

The safety and effectiveness of DIACOMIT have been established for the treatment of seizures associated with Dravet syndrome in patients taking clobazam who are 6 months and older and weighing 7 kg or more. Use of DIACOMIT in this pediatric population is supported by 2 multicenter placebo-controlled, double-blind randomized studies in patients 3 to 18 years of age with additional pharmacokinetic and safety data in patients 6 months to less than 3 years of age [see Clinical Studies (14)].

The safety and effectiveness of DIACOMIT have not been established in pediatric patients below the age of 6 months or who weigh less than 7 kg.

8.5 Geriatric Use

Clinical studies of DIACOMIT in Dravet syndrome did not include patients ≥65 years of age to determine whether they respond differently from younger patients. The possibility of age-associated hepatic and renal function abnormalities should be considered when using DIACOMIT in patients ≥65 years of age [see Clinical Pharmacology (12.3)].

8.6 Renal Impairment

There is no formal study of the pharmacokinetics and metabolism of DIACOMIT in patients with renal impairment. However, since DIACOMIT metabolites are eliminated mainly through the kidney, administration to patients with moderate or severe renal impairment is not recommended.

8.7 Hepatic Impairment

There has been no formal study of the pharmacokinetics of DIACOMIT in patients with liver impairment. However, since the drug is mainly metabolized by the liver, administration to patients with moderate or severe liver impairment is not recommended.

10 OVERDOSAGE

There are no data concerning overdose in humans. In mice treated with high doses of stiripentol (600 to 1800 mg/kg i.p.), decreased motor activity and decreased respiration were observed. Treatment of an overdose should be supportive (symptomatic measures in intensive care units).

For management of a suspected drug overdose, contact your regional Poison Control Center.

11 DESCRIPTION

Table 4. Description
Proprietary Name | DIACOMIT
Established Name | Stiripentol
Route of Administration | Oral
Chemical Name | 4,4-dimethyl-1-[3,4-(methylendioxyphenyl)-1-pentene-3-ol
Structural Formula

Stiripentol is a white to pale yellow crystalline powder with a bitter taste; it is practically insoluble in water (at 25°C), sparingly soluble in chloroform, and soluble in acetone, ethanol, ether, acetonitrile, and dichloromethane. The melting point is approximately 75°C. The pKa is 14.2, and measurement of the partition coefficient (water-octanol) provides a Log P value of 2.94. The molecular formula is C14H18O3 and the molecular weight is 234.3.

Capsules
DIACOMIT capsules contain 250 mg (size 2: pink) or 500 mg (size 0: white) of stiripentol. Capsules also contain the following inactive ingredients: erythrosine (250 mg capsule only), gelatin, indigotine (250 mg capsule only), magnesium stearate, povidone, sodium starch glycolate, titanium dioxide.

For Oral Suspension

DIACOMIT for oral suspension packets contain 250 mg or 500 mg of stiripentol. DIACOMIT packets also contain the following inactive ingredients: aspartame, carmellose sodium, erythrosine, glucose, hydroxyethylcellulose, povidone, sodium starch glycolate, sorbitol, titanium dioxide, fruit flavor (acacia, Bergamot oil, hypromellose, maltodextrin, sorbitol, and vanillin).

12 CLINICAL PHARMACOLOGY

12.1 Mechanism of Action

The mechanism by which DIACOMIT exerts its anticonvulsant effect in humans is unknown. Possible mechanisms of action include direct effects mediated through the gamma-aminobutyric acid (GABA)A receptor and indirect effects involving inhibition of cytochrome P450 activity with resulting increase in blood levels of clobazam and its active metabolite.

12.2 Pharmacodynamics

There are no relevant data on the pharmacodynamic effects of DIACOMIT.

12.3 Pharmacokinetics

The following pharmacokinetic properties of stiripentol have been found in studies in adult healthy volunteers and adult patients. Systemic exposure of stiripentol increases in a greater than dose proportional manner from 500 mg to 2000 mg.

Absorption: The median time to stiripentol peak plasma concentration is 2 to 3 hours.

Distribution: Protein binding of stiripentol is 99%.

Elimination: The elimination half-life of stiripentol ranges from 4.5 to 13 hours, increasing with doses of 500 mg, 1000 mg and 2000 mg.

Metabolism: On the basis of in vitro studies, the main liver cytochrome P450 (CYP) isoenzymes involved in metabolism are considered to be CYP1A2, CYP2C19, and CYP3A4.

Specific Populations The effect of age (≥ 65 years), race, renal and hepatic impairment on stiripentol pharmacokinetics is unknown [see Use in Specific Populations (8.5,8.6,8.7)]. Sex does not have a clinically significant effect on the pharmacokinetics of DIACOMIT.

Pediatric Patients: In a study of children (median age 7.3 years) with Dravet syndrome treated with DIACOMIT, valproate, and clobazam, the apparent clearance and volume of distribution of stiripentol were related to body weight. Elimination half-life increased from 8.5 hr (for 10 kg) to 23.5 hr (for 60 kg).

Drug Interaction Studies

In Vitro Studies
The metabolic pathway for stiripentol has not been clearly elucidated. Stiripentol is a substrate of several CYP enzymes, including CYP1A2, CYP2C19, and CYP3A4. Stiripentol inhibits and induces CYP1A2, CYP2B6, and CYP3A4. Stiripentol also inhibits CYP2C8, CYP2C19, and drug transporters, including P-gp and BCRP, at clinically relevant concentrations [see Drug Interactions (7.1)].

Clinical Studies
Antiepileptic drugs: Co-administration of clobazam with stiripentol increased concentrations of clobazam by approximately 2-fold and norclobazam (clobazam active metabolite) by 5-fold [see Drug Interactions (7.1)].

13 NONCLINICAL TOXICOLOGY

13.1 Carcinogenesis, Mutagenesis, Impairment of Fertility

Carcinogenesis
In mice, oral administration of stiripentol (0, 60, 200, or 600 mg/kg/day) for 78 weeks increased the incidences of liver tumors (hepatocellular adenoma and carcinoma) at the mid and high dose. The dose not associated with an increase in liver tumors (60 mg/kg/day) is less than the recommended human dose (RHD) of 50 mg/kg/day, based on body surface area (mg/m^2). In rats, oral administration of stiripentol at doses of up to 800 mg/kg/day (approximately 2.5 times the RHD on a mg/m^2 basis) for 102 weeks did not result in an increase in tumors.

Mutagenesis
Stiripentol was negative for genotoxicity in in vitro (Ames, HPRT gene mutation in V79 Chinese hamster cells, and chromosomal aberration in human lymphocytes) and in vivo (mouse bone marrow micronucleus) assays. Stiripentol was clastogenic in CHO cells in vitro, but only at cytotoxic concentrations.

Impairment of Fertility
Oral administration of stiripentol (0, 50, 200, or 800 mg/kg/day) to male and female rats prior to and throughout mating and continuing in females throughout organogenesis produced no adverse effects on fertility. The highest dose tested is approximately 2.5 times the RHD on mg/m^2 basis.

14 CLINICAL STUDIES

The effectiveness of DIACOMIT for the treatment of seizures associated with Dravet syndrome was established in 2 multicenter placebo-controlled double-blind randomized studies (Study 1 and Study 2), conducted according to similar protocols. To be enrolled in either study, patients were required to be 3 years to less than 18 years of age, to have Dravet syndrome (ILAE classification of epilepsy, 1989), and to be inadequately controlled on clobazam and valproate, with at least 4 generalized clonic or tonic-clonic seizures per month despite optimized therapy.

Eligible patients were enrolled in a 1-month baseline period during which they continued to receive their optimized antiepileptic treatment. Following this 1-month baseline, patients were randomly allocated to receive either DIACOMIT (fixed dose of 50 mg/kg/day in divided doses with no dose titration) or placebo, added to their treatment with clobazam and valproate. Duration of double-blind treatment was 2 months. The frequency of generalized clonic or tonic-clonic seizures during the study was recorded by patients and/or their caregivers, using a diary. Although patients with Dravet syndrome have several different types of seizures, only generalized clonic or tonic-clonic seizures were recorded, as other seizure types can be difficult to recognize by patients and/or their caregivers as seizures.

The primary efficacy endpoint for both studies was the responder rate. A responder was defined as a patient who experienced a greater than 50% decrease in the frequency (per 30 days) of generalized clonic or tonic-clonic seizures during the double-blind treatment period compared to the 4-week baseline period (i.e., placebo run-in). The mean change from baseline in frequency of generalized clonic or tonic clonic seizures was also evaluated.

In Study 1 (n=41), 21 patients were randomized to DIACOMIT, and 20 patients to placebo. In Study 2 (n=23), 12 patients were randomized to DIACOMIT, and 11 patients to placebo. In both studies, the demographic and baseline clinical characteristics were similar between the treatment groups.

Table5 summarizes the results of the primary endpoint for DIACOMIT in each study.

Table 5. Efficacy Results in the Intent-to-Treat Population in Study 1 and Study 2
 | Study 1; N=41 |  | Study 2; N=23
 | DIACOMIT N=21 | Placebo N=20 | DIACOMIT N=12 | Placebo N=11
Responder Analysisa
No of responders/total (Responder Rate) [95% CI] | 15/21 (71%) [52% – 91%] | 1/20 (5%) [0.0% – 15%] | 8/12 (67%) [40% – 93%] | 1/11 (9.1%) [0.0%– 26%]
p-valueb | <0.0001 |  | 0.0094e
Percentage Change from Baseline in Seizure Frequencyc
n Mean ± SD Median Min – Max | 20 -69% ± 42% -91% -100% – 28% | 16 7.6% ± 38% 7.4% -75% – 65% | 11 -74% ± 27% -81% -100% – -33% | 9 -13% ± 62% -27% -87% – 140%
p-valued | 0.0002 |  | 0.0056e
a Responder is defined as a patient with a greater than 50% decrease in frequency of generalized tonic-clonic or clonic seizures
b Fisher Exact Test
c Frequency of generalized tonic-clonic or clonic seizures during month 2
d Wilcoxon Test with two-sided t-approximation
e Nominal p value, as Study 2 was stopped early
CI=confidence interval; SD=standard deviation.

In both studies, the responder rate (primary efficacy endpoint) was significantly greater for DIACOMIT than for placebo. DIACOMIT was also superior to placebo for the reduction in mean frequency of generalized clonic or tonic-clonic seizures. In Study 1 and Study 2, respectively 43% and 25% of patients reported no generalized clonic or tonic-clonic seizure for the duration of the study.

Figure 1 displays the percentage of patients by category of percent reduction in tonic-clonic and clonic seizure frequency during month 2 of the treatment period compared to baseline (per 30 days) in Study 1 and Study 2 (pooled).

Figure 1.: Proportion of Patients by Category of Seizure Response for DIACOMIT and Placebo in Study 1 and Study 2 Pooled, Baseline to 2nd Month of Treatment (per 30 days).

The effectiveness of DIACOMIT for the treatment of seizures associated with Dravet syndrome in patients 6 months of age to less than 3 years of age was extrapolated from the demonstration of effectiveness in patients 3 years to less than 18 years of age in Study 1 and Study 2.

16 HOW SUPPLIED/STORAGE AND HANDLING

16.1 How Supplied

DIACOMIT Capsules

- 250 mg: size 2, pink, and imprinted with “Diacomit” and “250mg” are supplied as follows:
  Bottles of 60 NDC 68418-7939-6
- 500 mg: size 0, white, and imprinted with “Diacomit” and “500mg” are supplied as follows:
  Bottles of 60 NDC 68418-7940-6

For Oral Suspension

- 250 mg: pale pink fruit flavored powder packaged in packets are supplied as follows:
  Cartons of 60 NDC 68418-7941-6
- 500 mg: pale pink fruit flavored powder packaged in packets are supplied as follows:
  Cartons of 60 NDC 68418-7942-6

16.2 Storage and Handling

Store in a dry place at 20°C to 25°C (68°F to 77°F); excursions permitted to 15°C to 30°C (59°F to 86°F) [see USP Controlled Room Temperature]. Store in original package to protect from light.

17 PATIENT COUNSELING INFORMATION

Advise the patient to read the FDA-approved patient labeling (Medication Guide and Instructions for Use).

DIACOMIT Oral Capsule Administration
Inform patients or caregivers that DIACOMIT capsules must be swallowed whole with a glass of water during a meal. Capsules should not be broken or opened.

DIACOMIT For Oral Suspension Administration
DIACOMIT should be mixed in a glass of water and should be taken immediately after mixing during a meal [see Instructions for Use].

Somnolence

Advise patient or caregivers that somnolence may occur, and may require a decrease in the dose of clobazam [see Warnings and Precautions (5.1)]. Also, advise the patients and their caregivers to avoid alcohol consumption during DIACOMIT treatment [see Drug Interactions (7.3)].

If applicable, caution patients about hazardous machinery, including automobiles, until they know how DIACOMIT affects them.

Decreased Appetite and Decreased Weight
Advise patients or caregivers that decreased appetite is frequent and nausea and vomiting can also occur during DIACOMIT treatment, which can cause loss of weight [see Warnings and Precautions (5.2)].

Withdrawal Symptoms
Advise patients or caregivers that abrupt withdrawal of DIACOMIT may increase their risk of seizures or status epilepticus [see Dosage and Administration (2.5) and Warnings and Precautions (5.4)]. Instruct patients or caregivers to not discontinue use of DIACOMIT without consulting with their healthcare provider.

Neutropenia and Thrombocytopenia

Advise patients or caregivers of the risk of neutropenia and thrombocytopenia and the importance of hematologic testing, which should be obtained prior to starting treatment with DIACOMIT and then every 6 months [see Warnings and Precautions (5.3)].

Suicidal Thinking and Behavior
Counsel patients, their caregivers, and their families that AEDs, including DIACOMIT, may increase the risk of suicidal thoughts and behavior and advise them of the need to be alert for the emergence of worsening of symptoms of depression, any unusual changes in mood or behavior, or the emergence of suicidal thoughts, behavior, or thought of self-harm. Patients or caregivers should report behaviors of concern immediately to healthcare providers [see Warnings and Precautions (5.5)].

Use in Pregnancy
Advise patients to notify their healthcare provider if they become pregnant or intend to become pregnant during DIACOMIT therapy. Encourage patients to enroll in the NAAED Pregnancy registry if they become pregnant. This registry is collecting information about the safety of AEDs during pregnancy [see Use in Specific Populations (8.1)].

Use in Nursing
Instruct patients to notify their physician if they are breast feeding or intend to breast feed during therapy [see Use in Specific Populations (8.2)].

DIACOMIT Capsules and DIACOMIT for Oral Suspension manufactured by:
BIOCODEX
1, avenue Blaise Pascal
60000 BEAUVAIS
France

MEDICATION GUIDE

DIACOMIT (die-uh-KA-mit)

(stiripentol)

capsules, for oral use

for oral suspension

Read this Medication Guide before you start taking DIACOMIT and each time you get a refill. There may be new information.
This information does not take the place of talking to your healthcare provider about your medical condition or treatment.

What is the most important information I should know about DIACOMIT?
DIACOMIT can cause serious side effects, including:

1. Sleepiness and drowsiness. Sleepiness and drowsiness are serious and common side effects. DIACOMIT can make you sleepy or dizzy, and slow your thinking. Your healthcare provider may decrease your dose of clobazam or other seizure medicines.
  - Do not drive, operate heavy machinery, or do other dangerous activities until you know how DIACOMIT affects you.
  - Do not drink alcohol or take other medicines that may make you sleepy or dizzy while taking DIACOMIT until you talk to your healthcare provider.
  - DIACOMIT, when taken with alcohol or medicines that cause sleepiness or dizziness, may make your sleepiness or dizziness worse.
2. Loss of appetite and weight loss. Loss of appetite and weight loss are serious and common side effects. DIACOMIT can cause frequent nausea and loss of appetite that can cause weight loss.
  - Your weight should be checked frequently during DIACOMIT treatment.
  - Children who take DIACOMIT should have their weight and growth checked often.
3. Low white blood cell counts (neutropenia) and low platelet counts (thrombocytopenia). Low white blood cell counts may occur during treatment with DIACOMIT and may cause serious infections. Low platelet counts may cause serious bleeding problems. Your healthcare provider should check your white blood cell count and platelet count before and during treatment.
4. Do not stop taking DIACOMIT without first talking to your healthcare provider. Stopping a seizure medicine such as DIACOMIT should be done slowly to avoid having seizures more often, or seizures that do not stop (status epilepticus).
5. Like other antiepileptic drugs, DIACOMIT may cause suicidal thoughts or actions in a very small number of people (about 1 in 500).
  Call your healthcare provider right away if you have any of these symptoms, especially if they are new, worse, or worry you:
  - thoughts about suicide or dying
  - attempts to commit suicide
  - new or worse depression
  - new or worse anxiety
  - feeling agitated or restless
  - panic attacks
  - trouble sleeping (insomnia)
  - new or worse irritability
  - acting aggressive, being angry, or violent
  - acting on dangerous impulses
  - an extreme increase in activity and talking (mania)
  - other unusual changes in behavior or mood
  How can I watch for early symptoms of suicidal thoughts and actions?
  - Pay attention to any changes, especially sudden changes, in mood, behaviors, thoughts, or feelings.
  - Keep all follow-up visits with your healthcare provider as scheduled.

Call your healthcare provider between visits as needed, especially if you are worried about symptoms.
Suicidal thoughts or actions can be caused by things other than medicines. If you have suicidal thoughts or actions, your healthcare provider may check for other causes.
Call your healthcare provider right away if you have any of the above side effects while taking DIACOMIT.

What is DIACOMIT?

DIACOMIT is a prescription medicine used along with clobazam to treat seizures in people with Dravet syndrome who are 6 months of age and older and weighing 15 pounds (7 kg) or more.
DIACOMIT has not been shown to be able to treat seizures associated with Dravet syndrome without the use of clobazam.
It is not known if DIACOMIT is safe and effective in children under 6 months of age or who weigh less than 15 pounds (7 kg).

Before you take DIACOMIT, tell your healthcare provider about all of your medical conditions, including if you:

- have liver or kidney problems.
- have phenylkentonuria (PKU). DIACOMIT for oral suspension contains aspartame. The artificial sweetener may be harmful to people with PKU.
- have or have had depression, mood problems, suicidal thoughts or behavior.
- drink alcohol.
- are pregnant or plan to become pregnant. It is not known if DIACOMIT may harm your unborn baby.
  - Tell your healthcare provider right away if you become pregnant while taking DIACOMIT. You and your healthcare provider will decide if you should take DIACOMIT while you are pregnant.
  - Pregnancy Registry: If you become pregnant while taking DIACOMIT, talk to your healthcare provider about registering with the North American Antiepileptic Drug Pregnancy Registry. You can register by calling 1-888-233-2334. The purpose of this registry is to collect information about the safety of antiepileptic medicines, including DIACOMIT, during pregnancy. Information about the registry can be found at the website, http://www.aedpregnancyregistry.org/.
- are breastfeeding, or plan to breastfeed. It is not known if DIACOMIT passes into breast milk. Talk to your healthcare provider about the best way to feed your baby while taking DIACOMIT.

Tell your healthcare provider about all the medicines you take, including prescription and over-the-counter medicines, vitamins, and herbal supplements.
Taking DIACOMIT with certain other medicines can cause side effects or affect how well DIACOMIT or the other medicines work. Do not start or stop other medicines without talking to your healthcare provider. Know the medicines you take. Keep a list of them and show it to your healthcare provider and pharmacist when you get a new medicine.

How should I take DIACOMIT?

- Take DIACOMIT exactly as your healthcare provider tells you to take it.
- Your healthcare provider will tell you how much DIACOMIT to take and when to take it.
- DIACOMIT capsules should be swallowed whole with a glass of water during a meal. Do not break or open capsules.
- DIACOMIT for oral suspension should be mixed in a glass of water (100 mL) and should be taken right away after mixing during a meal. To be sure there is no medicine left in the glass, add a small amount of water (25 mL) to the drinking cup and drink all of the mixture. See the complete Instructions for Use on the right way to use DIACOMIT for oral suspension.
- Your healthcare provider may change your dose if needed. Do not change your dose of DIACOMIT without talking to your healthcare provider.
- If you miss a dose of DIACOMIT, take it as soon as you remember. If it is almost time for the next scheduled dose, skip the missed dose and take your next dose at your regular time. Do not take 2 doses of DIACOMIT at the same time.
- If you take too much DIACOMIT, call your healthcare provider or go to the nearest hospital emergency room right away.

What should I avoid while taking DIACOMIT?

- Do not drive, operate heavy machinery, or do other dangerous activities that need you to be alert until you know how DIACOMIT affects you.
- Do not drink alcohol or take other medicines that may make you sleepy or dizzy while taking DIACOMIT without first talking to your healthcare provider.

What are the possible side effects of DIACOMIT?
DIACOMIT may cause serious side effects, including:

- See “What is the most important information I should know about DIACOMIT?”

The most common side effects of DIACOMIT include:

- agitation
- loss of control of body movements (ataxia)
- low muscle tone or muscle weakness (hypotonia)
- nausea
- tremor
- trouble saying words clearly (dysarthria)
- trouble sleeping (insomnia)

These are not all the possible side effects of DIACOMIT. For more information, ask your healthcare provider or pharmacist.
Tell your healthcare provider if you have any side effect that bothers you or that does not go away.
Call your doctor for medical advice about side effects. You may report side effects to FDA at 1-800-FDA-1088.

How should I store DIACOMIT?

- Store DIACOMIT at room temperature between 68°F to 77°F (20°C to 25°C).
- Store in a dry place in the original package.
- Protect from light.

Keep DIACOMIT and all medicines out of the reach of children.

General information about the safe and effective use of DIACOMIT.
Medicines are sometimes prescribed for purposes other than those listed in a Medication Guide. Do not use DIACOMIT for a condition for which it was not prescribed. Do not give DIACOMIT to other people, even if they have the same symptoms that you have. It may harm them. You can ask your pharmacist or healthcare provider for information about DIACOMIT that is written for health professionals.

What are the ingredients in DIACOMIT?
Active ingredient: stiripentol
Capsule inactive ingredients: erythrosine (250 mg capsule only), gelatin, indigotine (250 mg capsule only), magnesium stearate, povidone, sodium starch glycolate, titanium dioxide.

For oral suspension inactive ingredients: aspartame, carmellose sodium, erythrosine, glucose, hydroxyethylcellulose, povidone, sodium starch glycolate, sorbitol, titanium dioxide, tutti frutti flavor.
Manufactured by:
BIOCODEX, 1 avenue Blaise Pascal, 60000 BEAUVAIS – France
For more information about DIACOMIT, go to www.biocodex.com or call BIOCODEX at 1-866-330-3050

Medication Guide has been approved by the U.S. Food and Drug Administration

Issued: 07/2022

INSTRUCTIONS FOR USE
DIACOMIT (die-uh-KA-mit)
(stiripentol)
for oral suspension

Be sure that you read, understand, and follow the Instructions for Use before preparing your child’s first dose of DIACOMIT for oral suspension and each time you get a refill. There may be new information. This information does not take the place of talking to your child’s healthcare provider about their medical condition or treatment. Ask your child’s healthcare provider or pharmacist if you have questions about how to mix or give a dose of DIACOMIT for oral suspension.

Important information:

- Your child’s healthcare provider will tell you the dose of DIACOMIT and how many packets are needed for your child’s dose.
- Each packet of DIACOMIT for oral suspension contains 250 mg or 500 mg of DIACOMIT as a powder. Be sure to use the right strength to prepare your child’s dose.
- When you receive DIACOMIT for oral suspension prescription at the pharmacy, check to make sure that you were given the right strength of DIACOMIT for oral suspension, the carton is not damaged, and the packets are not opened.
- Make sure you have enough packets of DIACOMIT for oral suspension to give a full dose. Call your healthcare provider if you need more DIACOMIT for oral suspension. Do not run out of your child’s medicine.
- Check that the expiration date on the carton (located on the bottom of the carton) and packet (located at the bottom right of the back side of the packet) has not passed. Do not use if the expiration date has passed.
- Talk with your child’s healthcare provider to help decide the best schedule for giving your child DIACOMIT for oral suspension.
- DIACOMIT for oral suspension must be mixed with water and your child must eat food right after taking DIACOMIT for oral suspension.
- Be sure to give the entire prepared dose of DIACOMIT for oral suspension to your child.
- For more information about DIACOMIT for oral suspension, see the “Medication Guide.”

Instructions for mixing DIACOMIT for oral suspension:

- Before you prepare a dose of DIACOMIT for oral suspension, check the prescription label on the carton for the number of packets you need to prepare a dose.
- Take the prescribed number of packets of DIACOMIT for oral suspension needed for the prescribed dose out of the carton.
- Wash and dry your hands before and after preparing DIACOMIT for oral suspension.
- When preparing DIACOMIT for oral suspension, choose a clean, flat work surface, and place the supplies you will need on the work surface.

Gather the following supplies:

- 1-spoon
- 1-measuring cup
- 1-small drinking cup
- water
- the correct number of DIACOMIT for oral suspension packets needed for the prescribed dose
- 1-clean pair of scissors

Step 1. Fill measuring cup with 100 mL of water.

Step 2. Pour 100 mL of water into the small drinking cup.

Step 3. Tap the packet of DIACOMIT for oral suspension to settle the medicine to the bottom of the packet.

Step 4. Using a clean pair of scissors, cut off the top of the packet and make sure the packet is fully open.

Step 5. Empty the packet into the small drinking cup.

- Look inside the packet to make sure there is no medicine left inside.
- If there is medicine left inside, hold the open end of the packet over your small drinking cup and tap the packet again to get all of the medicine out.

To make sure a full dose of DIACOMIT for oral suspension is given, it is important not to spill any medicine and that there is no medicine left in the packet.

Repeat Steps 3 through 5 for each packet of DIACOMIT for oral suspension needed for the total prescribed dose.

Step 6. Hold the small drinking cup with one hand. With your other hand, use the spoon to gently mix the medicine and the water until clear.

Steps 7 and 8 must be completed right after mixing the medicine.

Step 7. Have your child drink all of the mixture in the small drinking cup.

Step 8. To make sure there is no mixture left in the small drinking cup, add a small amount (25 mL) of water to the small drinking cup:

- Stir with the spoon.
- Repeat Step 7 above.

Step 9. Wash the small drinking cup and spoon. Allow the small drinking cup and spoon to dry. Throw away the empty packet and clean the work surface.

How should I store DIACOMIT for oral suspension?

- Store DIACOMIT for oral suspension at room temperature between 68°F to 77°F (20°C to 25°C).
- Store in the original package to protect from light.
- Do not open DIACOMIT for oral suspension packet until ready to use.
- Do not store the DIACOMIT mixture after it is mixed. It must be taken right after mixing.

Keep DIACOMIT for oral suspension and all medicines out of the reach of children.

This Instructions for Use has been approved by the U.S. Food and Drug Administration.

Manufactured by:
BIOCODEX, 1 avenue Blaise Pascal, 60000 BEAUVAIS – France

Approved: 7/2022

PACKAGE LABEL

NDC 68418-7939-6
DIACOMIT® 250 mg
(stiripentol)
Capsule
Attention Pharmacist: Dispense the enclosed Medication Guide to each patient
60 capsules
Rx Only
BIOCODEX
Active ingredient: Each capsule contains 250 mg stiripentol.
Directions for use: Swallow whole with a glass of water during a meal. DO NOT open, break or chew capsules. See full prescribing information for dosage and administration.
Warnings: Please refer to full prescribing information for further information.
Store at 20 to 25ºC (68 to 77ºF) in a dry place. Store in original package to protect from light. Keep out of the reach and sight of children.
*All trademark rights used under license
Manufactured by:
Biocodex, Gentilly, France
Distributed by:
Biocodex, Inc.
Bedminster, NJ 07921 USA

NDC 68418-7939-6
DIACOMIT® 250 mg
(stiripentol)
Capsule
Attention Pharmacist: Dispense the enclosed Medication Guide to each patient
60 capsules
BIOCODEX
Rx Only

NDC 68418-7939-6
DIACOMIT® 250 mg
(stiripentol)
Capsule
Attention Pharmacist: Dispense the enclosed Medication Guide to each patient
60 capsules
BIOCODEX
Rx Only
Peel here

Active ingredient: Each capsule contains 250 mg stiripentol.
Directions for use: Swallow whole with a glass of water during a meal. DO NOT open, break or chew capsules.
See full prescribing information for dosage and administration.
Warnings: Please refer to full prescribing information for further information.
Store at 20 to 25ºC (68 to 77ºF) in a dry place.
Store in original package to protect from light.
Keep out of the reach and sight of children.
Manufactured by:
Biocodex, Gentilly, France
Distributed by:
Biocodex, Inc.
Bedminster, NJ 07921 USA
*All trademark rights used under license

NDC 68418-7940-6
DIACOMIT® 500 mg
(stiripentol)
Capsule
Attention Pharmacist: Dispense the enclosed Medication Guide to each patient
60 capsules
Rx Only
BIOCODEX
Active ingredient: Each capsule contains 500 mg stiripentol.
Directions for use: Swallow whole with a glass of water during a meal. DO NOT open, break or chew capsules. See full prescribing information for dosage and administration.
Warnings: Please refer to full prescribing information for further information.
Store at 20 to 25ºC (68 to 77ºF) in a dry place. Store in original package to protect from light. Keep out of the reach and sight of children.
*All trademark rights used under license
Manufactured by:
Biocodex, Gentilly, France
Distributed by:
Biocodex, Inc.
Bedminster, NJ 07921 USA

NDC 68418-7940-6
DIACOMIT® 500 mg
(stiripentol)
Capsule
Attention Pharmacist: Dispense the enclosed Medication Guide to each patient
60 capsules
BIOCODEX
Rx Only

NDC 68418-7940-6
DIACOMIT® 500 mg
(stiripentol)
Capsule
Attention Pharmacist: Dispense the enclosed Medication Guide to each patient
60 capsules
BIOCODEX
Rx Only
Peel here

Active ingredient: Each capsule contains 500 mg stiripentol.
Directions for use: Swallow whole with a glass of water during a meal. DO NOT open, break or chew capsules.
See full prescribing information for dosage and administration.
Warnings: Please refer to full prescribing information for further information.
Store at 20 to 25ºC (68 to 77ºF) in a dry place.
Store in original package to protect from light.
Keep out of the reach and sight of children.
Manufactured by:
Biocodex, Gentilly, France
Distributed by:
Biocodex, Inc.
Bedminster, NJ 07921 USA
*All trademark rights used under license

NDC 68418-7941-6
DIACOMIT®
250 mg/packet
(stiripentol)
For oral suspension
Attention Pharmacist: Dispense the enclosed Medication Guide to each patient
60 Packets
Rx Only
BIOCODEX
Active ingredient: Each packet contains 250 mg stiripentol.
PHENYLKETONURICS: CONTAINS PHENYLALANINE - KEEP THIS AND ALL DRUGS OUT OF REACH OF CHILDREN.
Preparation: The powder should be mixed in a glass of water and should be taken immediately after mixing during a meal. See full prescribing information for dosage and administration.
Warnings: Please refer to full prescribing information for further information.
Store at 20 to 25ºC (68 to 77ºF) in a dry place. Store in original package to protect from light. Keep out of the reach and sight of children.
*All trademark rights used under license
Manufactured by:
Biocodex, Gentilly, France
Distributed by:
Biocodex, Inc.
Bedminster, NJ 07921 USA
30860/04

NDC 68418-7941-6
DIACOMIT®
250 mg/packet
(stiripentol)
For oral suspension
Rx Only
BIOCODEX
See accompanying prescribing information for complete dosage and administration information. This packet contains 250 mg of stiripentol.
PHENYLKETONURICS: CONTAINS PHENYLALANINE - KEEP THIS AND ALL DRUGS OUT OF REACH OF CHILDREN - This packet is not child-resistant.
Preparation: The powder should be mixed in a glass of water and should be taken immediately after mixing during a meal.
*All trademark rights used under license
Store at 20 to 25ºC (68 to 77ºF)
Manufactured by Biocodex France
Lot:
EXP:
5560/03

NDC 68418-7942-6
DIACOMIT®
500 mg/packet
(stiripentol)
For oral suspension
Attention Pharmacist: Dispense the enclosed Medication Guide to each patient
60 Packets
Rx Only
BIOCODEX
Active ingredient: Each packet contains 500 mg stiripentol.
PHENYLKETONURICS: CONTAINS PHENYLALANINE - KEEP THIS AND ALL DRUGS OUT OF REACH OF CHILDREN.
Preparation: The powder should be mixed in a glass of water and should be taken immediately after mixing during a meal. See full prescribing information for dosage and administration.
Warnings: Please refer to full prescribing information for further information.
Store at 20 to 25ºC (68 to 77ºF) in a dry place. Store in original package to protect from light. Keep out of the reach and sight of children.
*All trademark rights used under license
Manufactured by:
Biocodex, Gentilly, France
Distributed by:
Biocodex, Inc.
Bedminster, NJ 07921 USA
30870/04

NDC 68418-7942-6
DIACOMIT®
500 mg/packet
(stiripentol)
For oral suspension
Rx Only
BIOCODEX
See accompanying prescribing information for complete dosage and administration information. This packet contains 250 mg of stiripentol.
PHENYLKETONURICS: CONTAINS PHENYLALANINE - KEEP THIS AND ALL DRUGS OUT OF REACH OF CHILDREN - This packet is not child-resistant.
Preparation: The powder should be mixed in a glass of water and should be taken immediately after mixing during a meal.
*All trademark rights used under license
Store at 20 to 25ºC (68 to 77ºF)
Manufactured by Biocodex France
Lot:
EXP:
5570/03